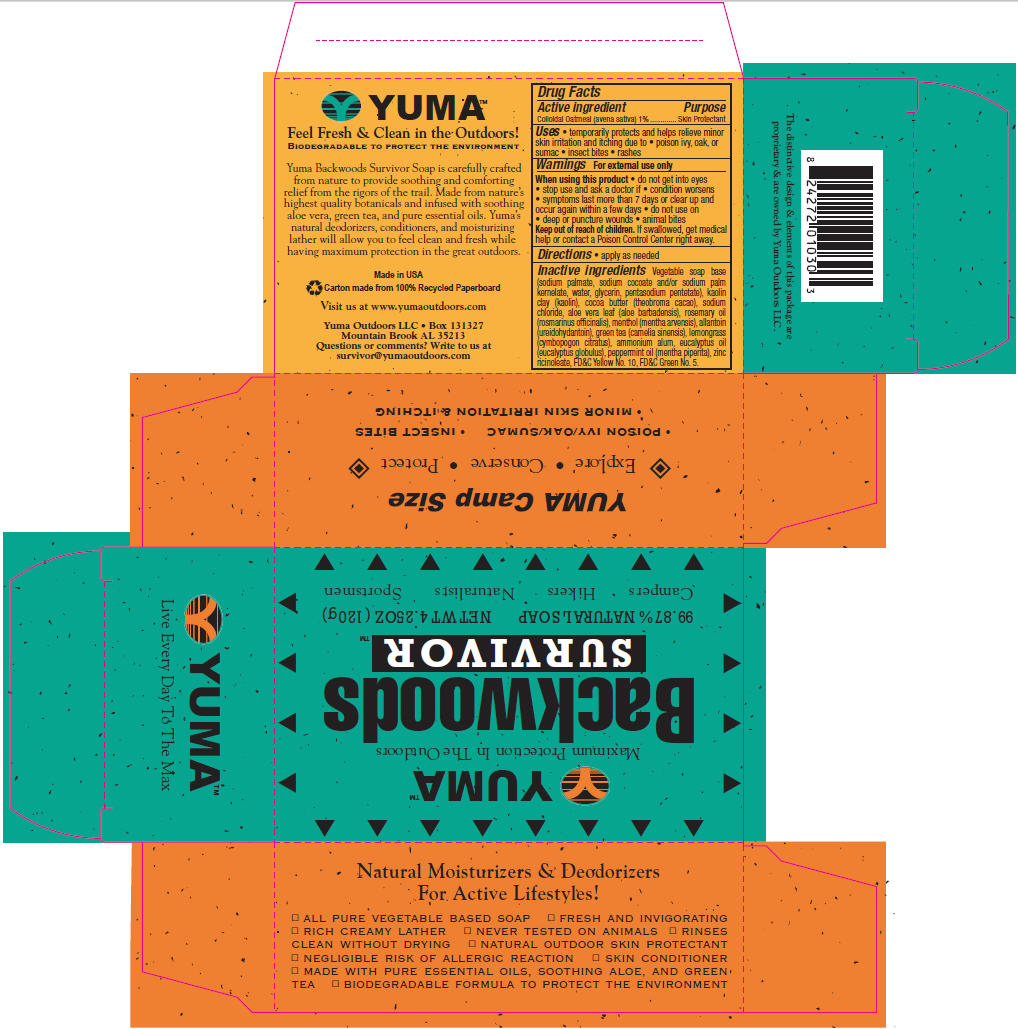 DRUG LABEL: Yuma
NDC: 75933-1425 | Form: SOAP
Manufacturer: Yuma Outdoors LLC
Category: otc | Type: HUMAN OTC DRUG LABEL
Date: 20110105

ACTIVE INGREDIENTS: OATMEAL 1.205 g/1 1
INACTIVE INGREDIENTS: ALOE; ROSEMARY; MENTHA ARVENSIS FLOWER OIL; ALLANTOIN; CAMELLIA SINENSIS ROOT; WEST INDIAN LEMONGRASS OIL; POTASSIUM ALUM; EUCALYPTUS OIL; PEPPERMINT OIL; ZINC RICINOLEATE; D&C YELLOW NO. 10; D&C GREEN NO. 5; SODIUM COCOATE; SODIUM PALM KERNELATE; WATER; GLYCERIN; PENTASODIUM PENTETATE; KAOLIN; COCOA BUTTER; SODIUM CHLORIDE

Drug Facts

Active Ingredients

Colloidal Oatmeal (avena sativa) 1%

Purpose

Skin Protectant

INDICATIONS AND USAGE

Uses • temporarily protects and helps relieve minor skin irritation and itching due to •poison ivy, oak or sumac •insect bites •rashes

Warnings For external use only

When using this product •do not get into eyes •stop use and ask a doctor if •condition worsens •symptoms last more than 7 days or clear up and occur again within a few days

•do not use on •deep or puncture wounds •animal bites

Keep out of reach of children. If swallowed, get medical help or contact a Poison Control Center right away.

DOSAGE AND ADMINISTRATION

Directions •apply as needed

INACTIVE INGREDIENT

Inactive Ingredients Vegetable soap base (sodium palmate, sodium cocoate and/or sodium palm kemelate, water, glycerin, pentasodium pentetate), kaolin clay (kaolin), cocoa butter (theobroma cacao), sodium chloride, aloe vera leaf (aloe barbadensis), rosemary oil (rosmarinus officinalis), menthol (mentha arvensis), allantoin (ureidohydantoin), green tea (camelia sinensis), lemongrass (cymbopogon citratus), ammonium alum, eucalyptus oil (eucalyptus globulus), peppermint oil (mentha piperita), zinc ricinoleate, FD&C Yellow No. 10, FD&C Green No. 5.

PACKAGE LABEL

Package Label - Principal Display Panel – Yuma Backwoods Survivor Carton